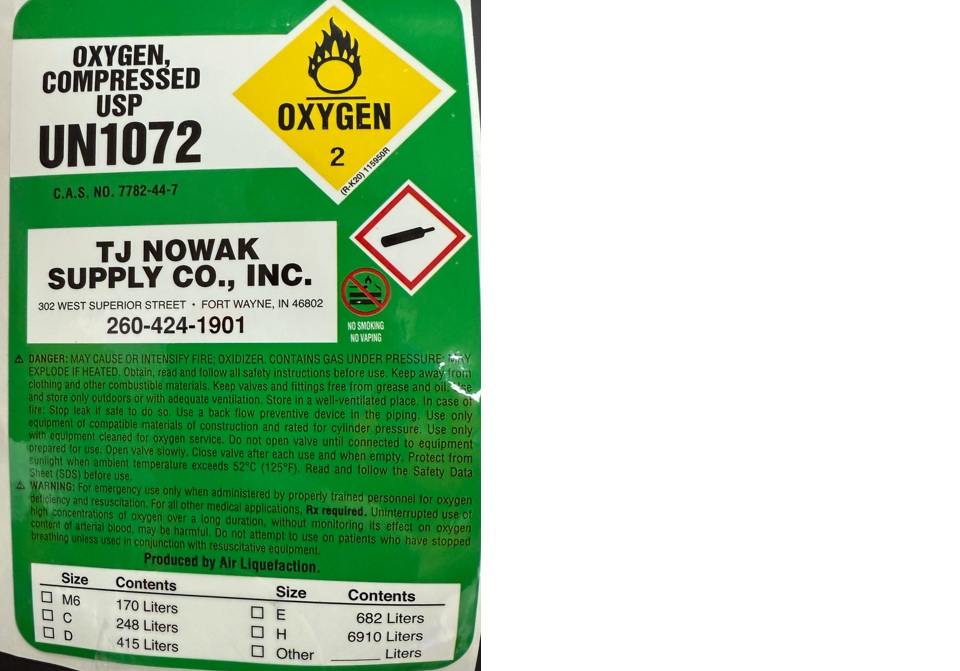 DRUG LABEL: Oxygen
NDC: 64952-002 | Form: GAS
Manufacturer: T J Nowak Supply Co Inc
Category: prescription | Type: HUMAN PRESCRIPTION DRUG LABEL
Date: 20251210

ACTIVE INGREDIENTS: OXYGEN 990 mL/1 L

oxygen

PACKAGE LABEL

OXYGEN, COMPRESSED USP

UN1072

C.A.S. NO. 7782-44-7

TJ NOWAK SUPPLY CO., INC.

302 WEST SUPERIOR STREET FORT WAYNE, IN 46802

260-424-1901

NO SMOKING

NO VAPING

DANGER: MAY CAUSE OR INTENSIFY FIRE; OXIDIZER. CONTAINS GAS UNDER PRESSURE; MAY EXPLODE IF HEATED. Obtain, read and follow all safety instructions before use. Keep away from clothing and other combustible materials. Keep valves and fittings free from grease and oil. Use and store only outdoors or with adequate ventilation. Store in a well-ventilated place. In case of fire: Stop leak if safe to do so. Use a back flow preventive device in the piping. Use only equipment cleaned for oxygen service. Do not open valve until connected to equipment prepared for use. Open valve slowly. Close valve after each use and when empty. Protect from sunlight when ambient temperature exceeds 52 C (125 F). Read and follow the Safety Data Sheet (SDS) before use.

WARNING: For emergency use only when administered by properly trained personnel for oxygen deficiency and resuscitation. For all other medical applications, Rx required. Uninterrupted use of high concentrations of oxygen over a long duration, without monitoring its effect on oxygen content of arterial blood, may be harmful. Do not attempt to use on patients who have stopped breathing unless used in conjunction with resuscitative equipment.

Produced by Air Liquefaction.

Size Contents Size Contents

M6 170 Liters E 682 Liters

C 248 Liters H 6910 Liters

D 415 Liters Other Liters